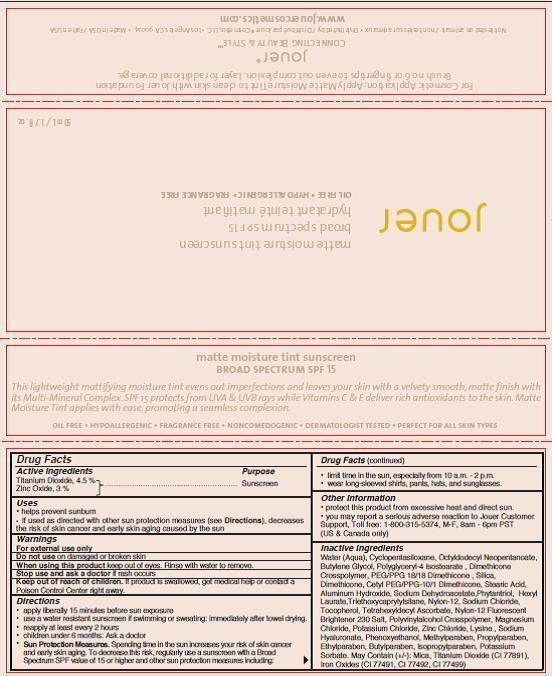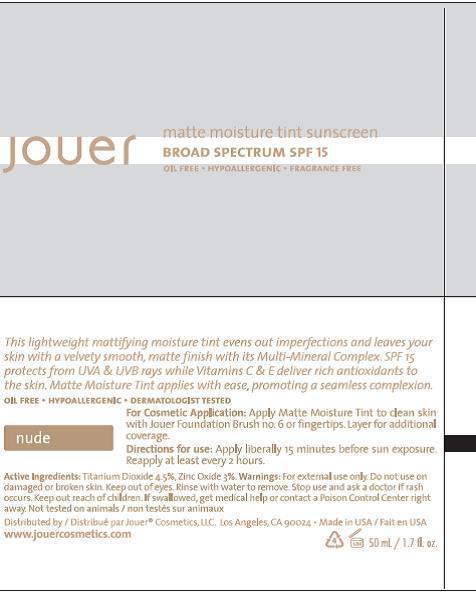 DRUG LABEL: MATTE MOISTURE TINT SUNSCREEN BROAD SPECTRUM SPF 15
NDC: 69017-202 | Form: CREAM
Manufacturer: Jouer Cosmetics LLC
Category: otc | Type: HUMAN OTC DRUG LABEL
Date: 20140729

ACTIVE INGREDIENTS: TITANIUM DIOXIDE 4.5 mg/100 mL; ZINC OXIDE 3.0 mg/100 mL
INACTIVE INGREDIENTS: WATER; CYCLOMETHICONE 5; OCTYLDODECYL NEOPENTANOATE; BUTYLENE GLYCOL; POLYGLYCERYL-4 ISOSTEARATE; SILICON DIOXIDE; DIMETHICONE; CETYL PEG/PPG-10/1 DIMETHICONE (HLB 4); STEARIC ACID; ALUMINUM HYDROXIDE; SODIUM DEHYDROACETATE; PHYTANTRIOL; HEXYL LAURATE; TRIETHOXYCAPRYLYLSILANE; NYLON-12; SODIUM CHLORIDE; TOCOPHEROL; TETRAHEXYLDECYL ASCORBATE; MAGNESIUM CHLORIDE; POTASSIUM CHLORIDE; ZINC CHLORIDE; LYSINE; HYALURONATE SODIUM; PHENOXYETHANOL; METHYLPARABEN; PROPYLPARABEN; ETHYLPARABEN; BUTYLPARABEN; ISOPROPYLPARABEN; POTASSIUM SORBATE; MICA; FERRIC OXIDE RED; FERRIC OXIDE YELLOW; FERROSOFERRIC OXIDE

matte moisture tint sunscreen broard spectrum SPF 15 "Nude"

ACTIVE INGREDIENT

Titanium Dioxide 4.5%

Zinc Oxide 3.0%

PURPOSE

Sunscreen

Uses

Helps prevent sunburns

If used as directed with other sun protection measures (see Directions), decreases the risk of skin cancer and early skin aging caused by the sun.

Warnings

WARNINGS

For external use only

Do not use on damages or broken skin

Stop use and ask a doctor if rash occurs

When using this product keep out of eyes. Rinse with water to remove.

Keep out of reach of children. If swallowed, get medical help or contact a poison control center right away

Directions

apply liberally 15 minutes before sun exposure

use a water resistant sunscreen if swimming or sweating: Immediately after towel drying.

reapply at least every 2 hours.

Children under 6 months. Ask a doctor

Sun Protection Measures. Spending time in the sun increases your risk of skin cancer

and early skin aging. To decrease this risk, regularly use a sunscreen with a Broad

Spectrum SPF value of 15 or higher and other sun protection measure including:

limit time in the sun, especially from 10 a.m. to 2 p.m.

wear long-sleeved shirts, pants, hats, and sunglasses

OTHER SAFETY INFORMATION

protect this product from excessive heat and direct sun.

ADVERSE REACTIONS

-you may report a serious adverse reaction to Jouer Customer support, toll free: 1-800-315-5374, M-F, 8am-6pm PST (US and Canada Only)

INACTIVE INGREDIENT

INACTIVE INGREDIENTS: WATER (AQUA), CYCLOPENTASILOXANE, OCTYLDODECYL NEOPENTANOATE, BUTYLENE GLYCOL, POLYGLYCERYL-4 ISOSTEARATE, DIMETHICONE CROSSPOLYMER, PEG/PPG 18/18 DIMETHICONE, SILICA, DIMETHICONE, CETYL PEG/PPG-10/1 DIMETHICONE, STEARIC ACID, ALUMINUM HYDROXIDE, SODIUM DEHYDROACETATE, PHYTANTRIOL, HEXYL LAURATE, TRIETHOXYCAPRYLYLSILANE, NYLON-12, SODIUM CHLORIDE, RETINYL PALMITATE, TOCOPHEROL, TETRAHEXYLDECYL ASCORBATE, POLYDODECANAMIDEAMINIUM TRIAZADIPHENYLETHENESULFONATE, POLYVINYLALCOHOL CROSSPOLYMER, MAGNESIUM CHLORIDE, POTASSIUM CHLORIDE, ZINC CHLORIDE, LYSINE, SODIUM HYALURONATE, PHENOXYETHANOL, METHYLPARABEN, PROPYLPARABEN, ETHYLPARABEN, BUTYLPARABEN, ISOPROPYLPARABEN, POTASSIUM SORBATE. MAY CONTAIN (+/-): MICA, TITANIUM DIOXIDE (CI 77891), IRON OXIDES (CI 77491, CI 77492, CI 77499).